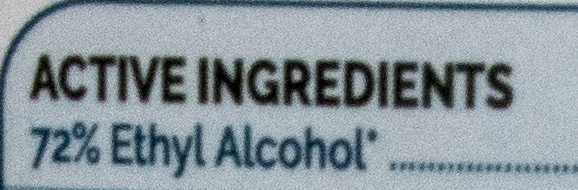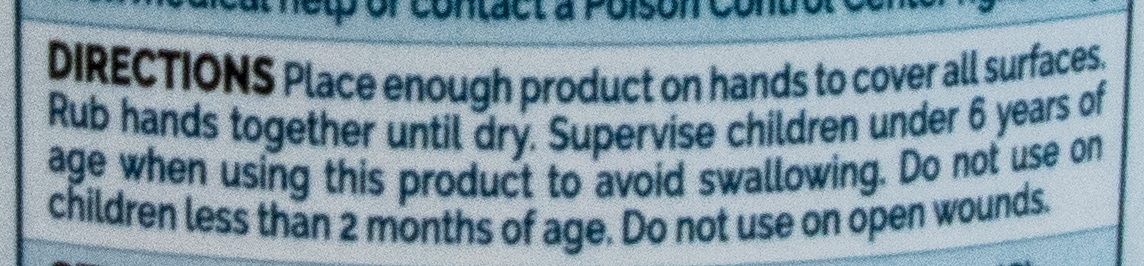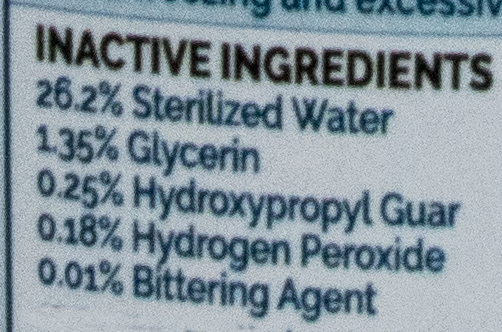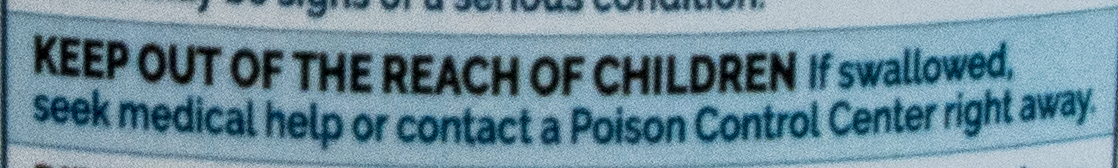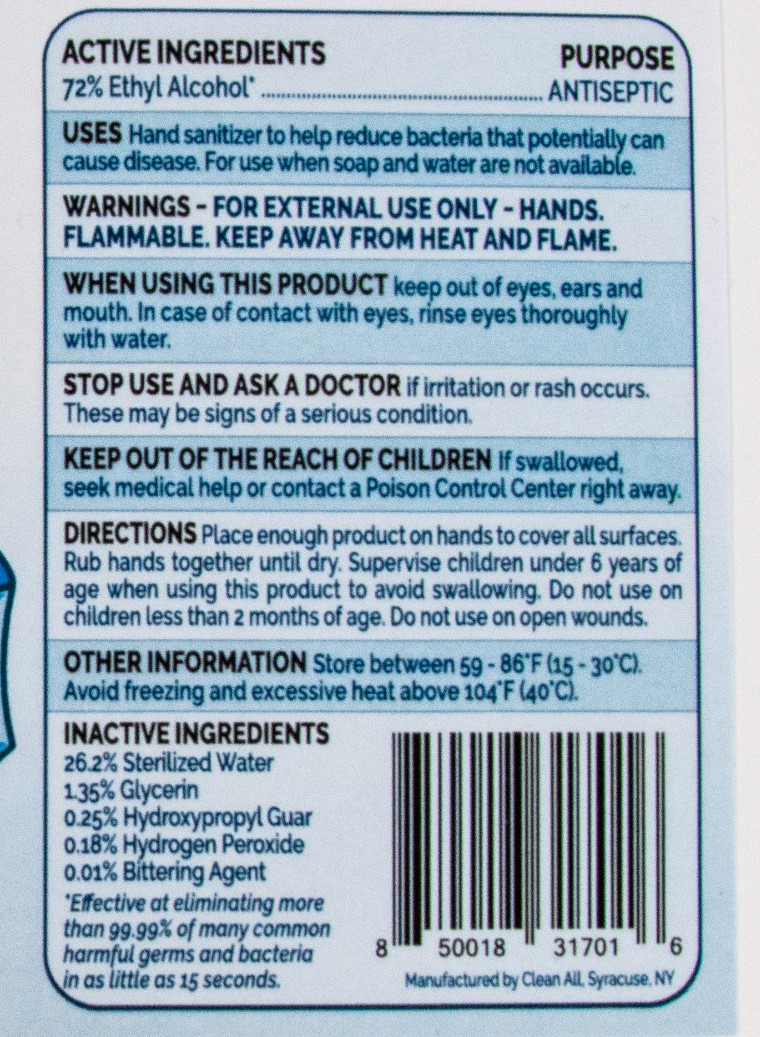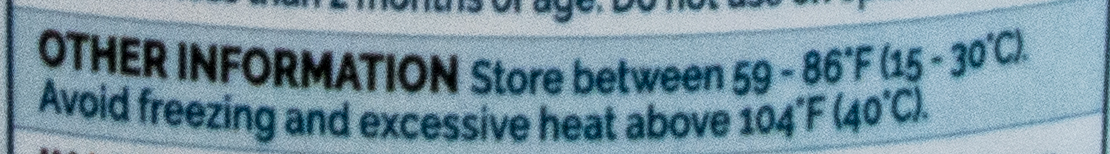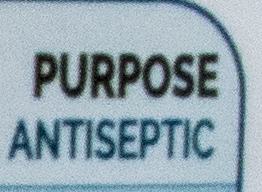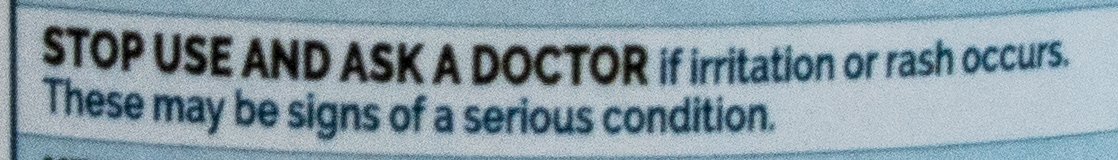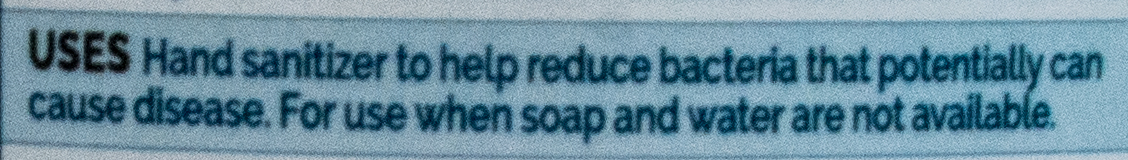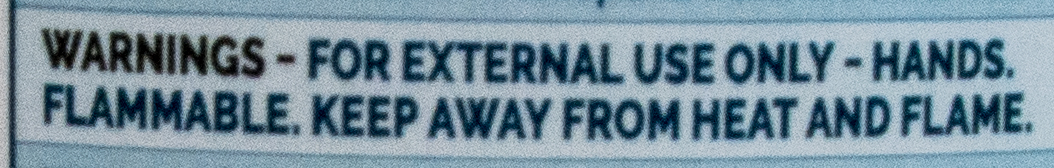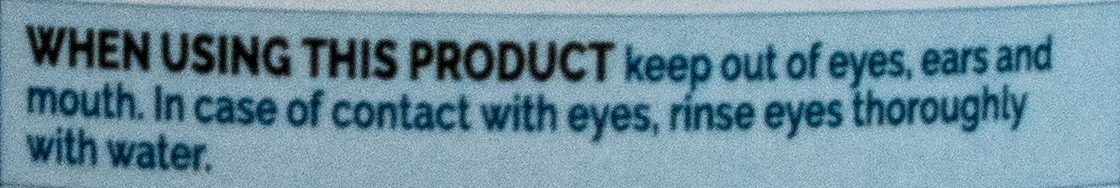 DRUG LABEL: Hand Sanitizer Gel
NDC: 75660-002 | Form: GEL
Manufacturer: Solvents and Petroleum Service, Inc.
Category: otc | Type: HUMAN OTC DRUG LABEL
Date: 20200623

ACTIVE INGREDIENTS: ALCOHOL 72 mL/100 mL
INACTIVE INGREDIENTS: DENATONIUM BENZOATE 0.01 mL/100 mL; GLYCERIN 1.35 mL/100 mL; HYDROGEN PEROXIDE 0.18 mL/100 mL; WATER 26.2 mL/100 mL; HYDROXYPROPYL GUAR (2500-4500 MPA.S AT 1%) 0.25 mL/100 mL

Active Ingredients

72% Ethyl Alcohol

Purpose

Antiseptic, Hand Sanitizer

Use

Uses Hand Sanitizer to help reduce bacteria that potentially can cause disease. For use when soap and water are not available.

Warnings

For external use only. Flammable. Keep away from heat or flame

Do not use

- in children less than 2 months of age
- on open skin wounds

When using this product keep out of eyes, ears, and mouth. In case of contact with eyes, rinse eyes thoroughly with water.

STOP USE AND ASK A DOCTOR if irritation or rash occurs. These may be signs of a serious condition.

Keep OUT OF THE REACH OF CHILDREN

Keep out of reach of children. If swallowed, get medical help or contact a Poison Control Center right away.

Directions

- Place enough product on hands to cover all surfaces. Rub hands together until dry.
- Supervise children under 6 years of age when using this product to avoid swallowing.

Other information

- Store between 15-30C (59-86F)
- Avoid freezing and excessive heat above 40C (104F)

Inactive ingredients

glycerin, hydrogen peroxide, purified water USP